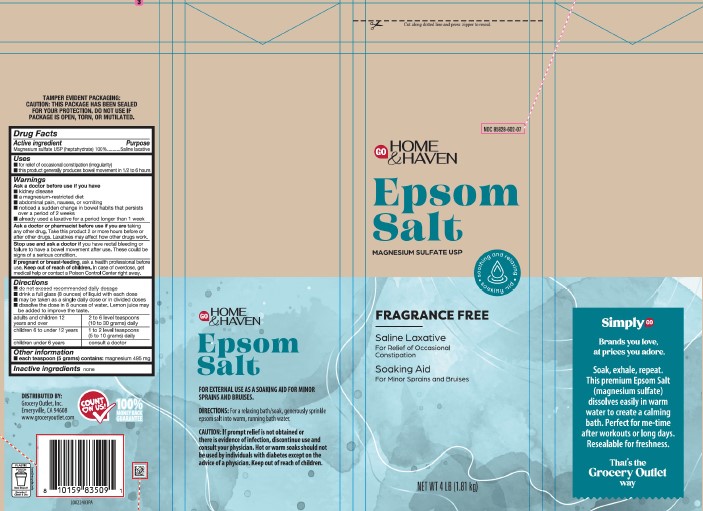 DRUG LABEL: Epsom Salt
NDC: 85828-602 | Form: GRANULE, FOR SOLUTION
Manufacturer: Grocery Outlet, Inc.
Category: otc | Type: HUMAN OTC DRUG LABEL
Date: 20260204

ACTIVE INGREDIENTS: MAGNESIUM SULFATE HEPTAHYDRATE 1 g/1 g

GO HOME & HAVEN 602.002/602AA
Epsom Salt

Tamper Evident Statement

TAMPER EVIDENT PACKAGING:

CAUTION: THIS PACKAGE HAS BEEN SEALED FOR YOUR PROTECTION. DO NOT USE IF PACKAGE IS OPEN, TORN, OR MUTILATED.

Active ingredient

Magnesium sulfate USP (heptahydrate) 100%

Purpose

Saline laxative

Uses

- for relief of occasional constipation (irregularity)
- this product generally produces bowel movement in ½ to 6 hours

Warnings

for this product

Ask a doctor before use if you have

- kidney disease
- a magnesium-restricted diet
- abdominal pain, nausea, or vomiting
- noticed a sudden change in bowel habits that persists over a period of 2 weeks
- already used a laxative for a period longer than 1 week

Ask a doctor or pharmacist before use if you are

taking any other drug. Take this product 2 or more hours before or after other drugs. Laxatives may affect how other drugs work.

Stop use and ask a doctor if

you have rectal bleeding or failure to have a bowel movement after use. These could be signs of a serious condition.

If pregnant or breast-feeding,

ask a health professional before use.

Keep out of reach of children.

In case of overdose, get medical help or contact a Poison Control Center right away.

Directions

- do not exceed recommended daily dosage
- drink a full glass (8 ounces) of liquid with each dose
- may be taken as a single daily dose or in divided doses
- dissolve the dose in 8 ounces of water. Lemon juice may be added to improve the taste.

adults and children 12 years and over: 2 to 6 level teaspoons (10 to 30 grams) daily

children 6 to under 12 years: 1 to 2 level teaspoons (5 to 10 grams) daily

children under 6 years: consult a doctor

Other information

- each teaspoon (5 grams) contains: magnesium 495 mg

Inactive ingredients

none

Side Panel Claims

GO HOME & HAVEN

Epsom Salt

FOR EXTERNAL USE AS A SOAKING AID FOR MINOR SPRAINS AND BRUISES.

DIRECTIONS: For a relaxing bath/soak, generously sprinkle epsom salt into warm, running bath water.

CAUTION: If prompt relief is not obtained or there is evidence of infection, discontinue use and consult your physican. Hot or warm soaks should not be used by individuals with diabetes except on the advice of a physican. Keep out of reach of children.

Simply GO

Brands you love, at prices you adore.

Soak, exhale, repeat.

This premium Epsom Salt (magnesium sulfate) dissolves easliy in warm water to create a calming bath. Perfect for me-time after workouts or long days. Resealable for freshness.

That's the Grocery Outlet way.

Adverse Reaction

DISTRIBUTED BY:

Grocery Outlet, Inc.

Emeryville, CA 94608

www.groceryoutlet.com

COUNT ON US

100% MONEY BACK GUARANTEE

PLASTIC

POUCH

Store Drop-off

Recycle if Clean & Dry

how2recycle.info

Principal Display Panel

Cut along dotted line and press zipper to reseal.

NDC 85828-602-07

GO HOME & HAVEN

Epsom Salt

MAGNESIUM SULFATE USP

FRAGRANCE FREE

- soothing and relaxing
- soaking aid

Saline Laxative

For Relief of Occasional Constipation

Soaking Aid

For Minor Sprains and Bruises

NET WT 4 LB (1.81 kg)